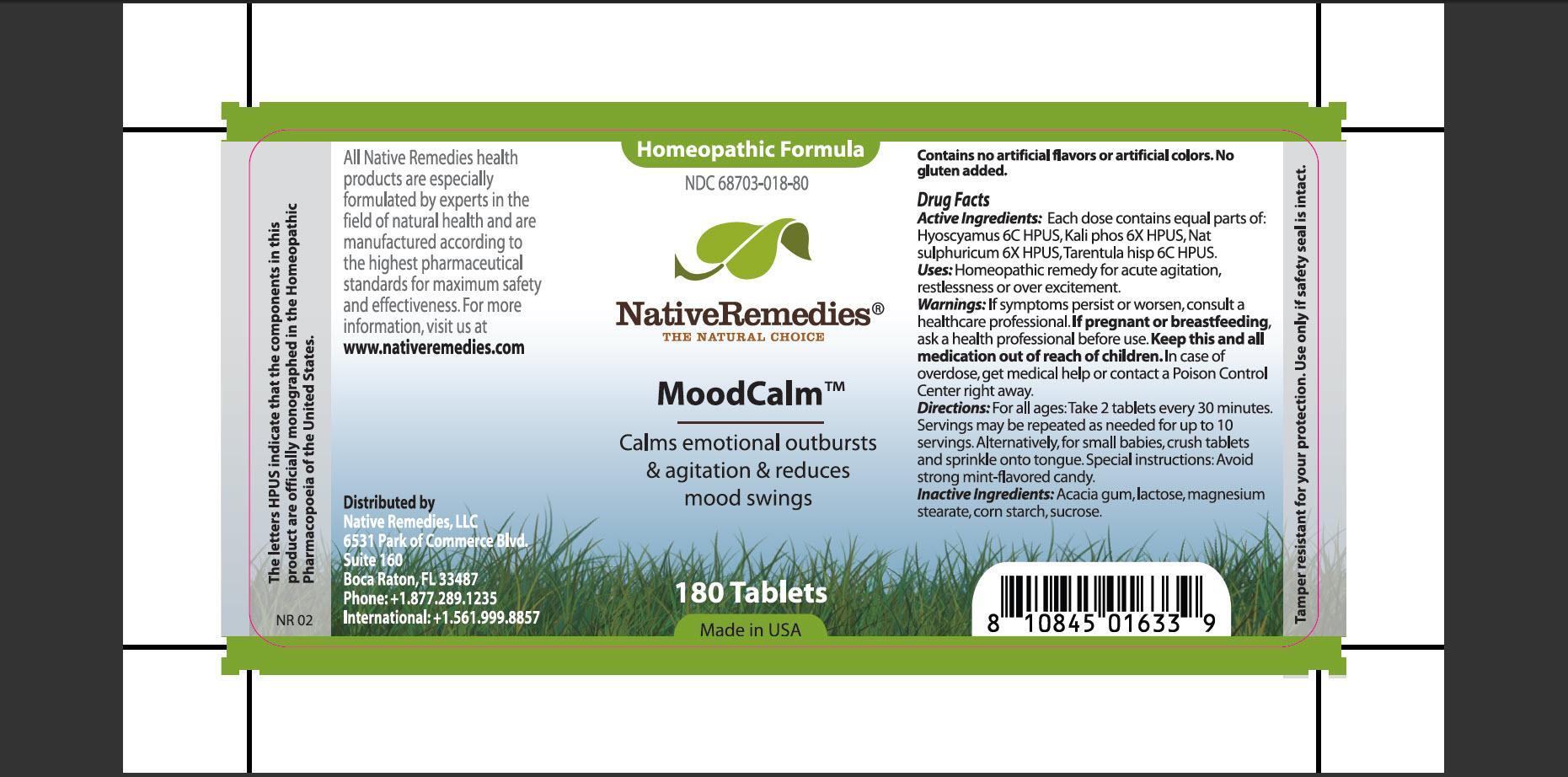 DRUG LABEL: MoodCalm
NDC: 68703-018 | Form: TABLET
Manufacturer: Silver Star Brands, Inc
Category: homeopathic | Type: HUMAN OTC DRUG LABEL
Date: 20150716

ACTIVE INGREDIENTS: HYOSCYAMUS NIGER 6 [hp_C]/1 1; POTASSIUM PHOSPHATE, DIBASIC 6 [hp_X]/1 1; SODIUM SULFATE 6 [hp_X]/1 1; LYCOSA TARANTULA 6 [hp_C]/1 1
INACTIVE INGREDIENTS: ACACIA; LACTOSE; MAGNESIUM STEARATE; STARCH, CORN; SUCROSE

MoodCalm

PURPOSE

Calms emotional outbursts and agitation and reduces mood swings

ACTIVE INGREDIENT

Active Ingredients:Each dose contains equal parts of: Hyoscyamus 6C HPUS, Kali phos 6X HPUS, Nat sulphuricum 6X HPUS, Tarentula hisp 6C HPUS

INDICATIONS AND USAGE

Uses: Homeopathic remedy for acute agitation, restlessness or over excitement

WARNINGS

Warnings: If symptoms persist or worsen, consult a healthcare professional

PREGNANCY OR BREAST FEEDING

If pregnant of breastfeeding, ask a health professional before use

KEEP OUT OF REACH OF CHILDREN

Keep this and all medication out of reach of children

OVERDOSAGE

In case of overdose, get medical help or contact a Poison Control Center right away

DOSAGE AND ADMINISTRATION

Directions: For all ages: Take 2 tablets every 30 minutes. Serving may be repeated as needed for up to 10 servings. Alternatively, for small babies, crush tablets and sprinkle onto tongue. Special instructions: Avoid strong mint-flavored candy

INACTIVE INGREDIENT

Inactive Ingredients: Acacia gum, lactose, magnesium stearate, corn starch, sucrose

PATIENT COUNSELING INFORMATION

The letters HPUS indicate that the components in this product are officially monographed in the Homeopathic Pharmacopoeia of the United States.

All Native Remedies health products are especially formulated by experts in the field of natural health and are manufactured according to the highest pharmaceutical standards for maximum safety and effectiveness. For more information, visit us at www.nativeremedies.com

Distributed by
Native Remedies, LLC
6531 Park of Commerce Blvd.
Siute 160
Boca Raton, FL 33487
Phone: +1.877.289.1235
International:+1.561.999.8857

Contains no artificial flavors or artificial colors. No gluten added

STORAGE AND HANDLING

Tamper resistant for your protection. Use only if safety seal is intact.